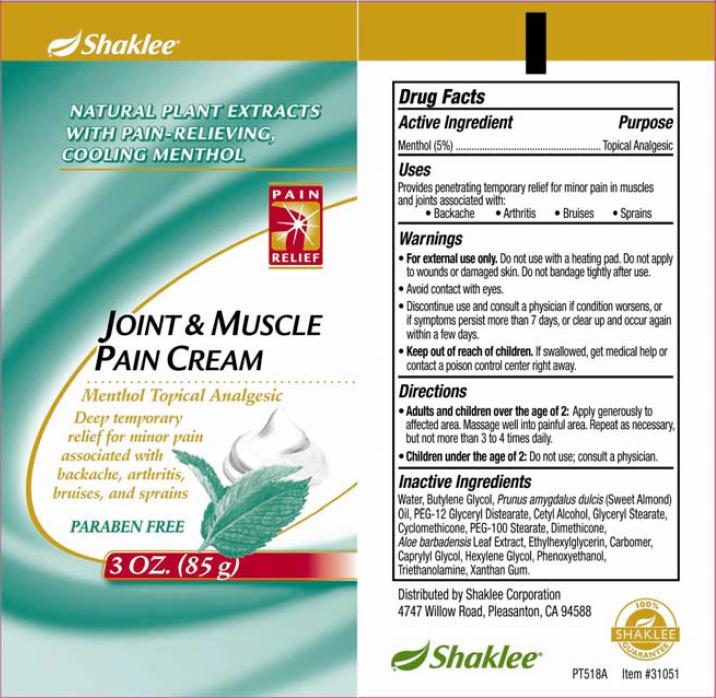 DRUG LABEL: Joint and Muscle Pain
NDC: 55379-404 | Form: CREAM
Manufacturer: BioZone Laboratories, Inc.
Category: otc | Type: HUMAN OTC DRUG LABEL
Date: 20100728

ACTIVE INGREDIENTS: Menthol 50 mg/1 g

Drug Facts

ACTIVE INGREDIENT

Menthol (5%)

PURPOSE

Topical Analgesic

Directions

Provides penetrating temporary relief for minor pain in muscles and joints associated with:

- Backache
- Arthritis
- Bruises
- Sprains

Warnings

- For external use only. Do not use with a heating pad. Do not apply to wounds or damaged skin. Do not bandage tightly after use.
- Avoid contact with eyes.
- Discontinue use and consult a physician if condition worsens, or if symptoms persist more than 7 days, or clear up and occur again within a few days.
- Keep out of reach of children. if swallowed, get medical help or contact a poison control center right away.

Directions

- Adults and children over the age of 2: Apply generously to affected area. Massage well into painful area. Repeat as necessary, but not more than 3 to 4 times daily.
- Children under the age of 2: Do not use; consult a physician.

Inactive Ingredients

Water, Butylene Glycol, Prunus amygdalus dulcis (Sweet Almond) Oil, PEG-12 Glyceryl Distearate, Cetyl Alcohol, Glyceryl Stearate, Cyclomethicone, PEG-100 Stearate, Dimethicone, Aloe barbadensis Leaf Extract, Ehtylhexylglycerin, Carbomer, Caprylyl Glycol, Hexylene Glycol, Phenoxyethanol, Triethanolamine, Xanthan Gum.

PACKAGE LABEL

Image: tube_shk10_1.jpg